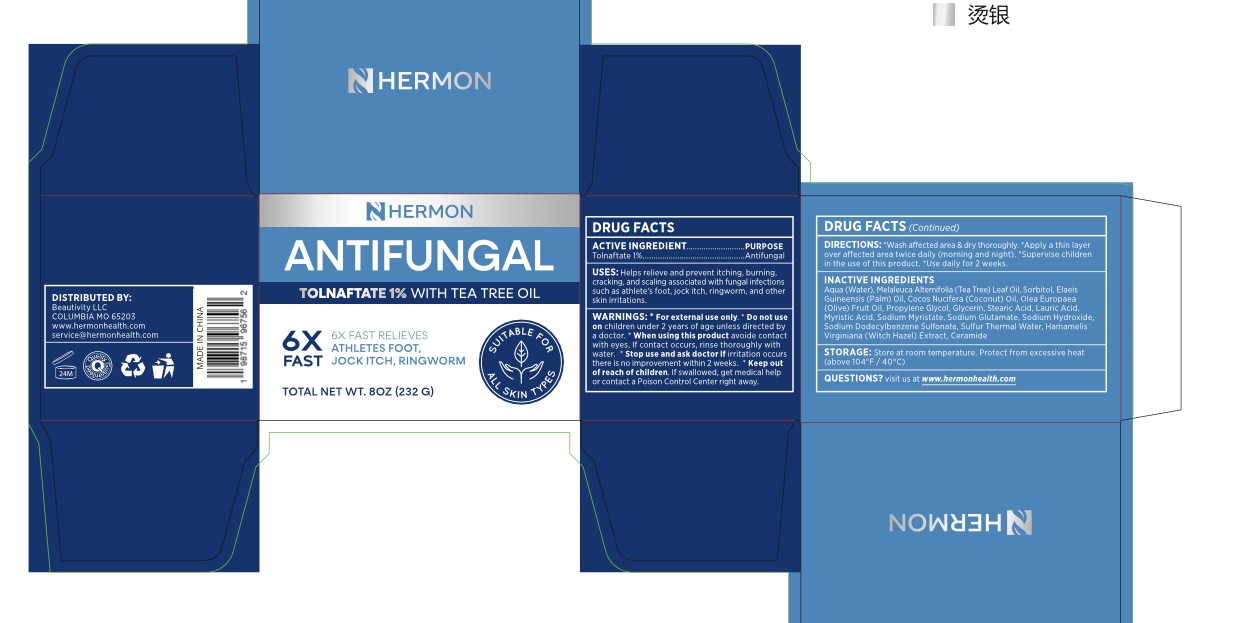 DRUG LABEL: Athlete Foot Medicated bar
NDC: 85398-007 | Form: SOAP
Manufacturer: Beautivity LLC
Category: otc | Type: HUMAN OTC DRUG LABEL
Date: 20251021

ACTIVE INGREDIENTS: TOLNAFTATE 1 g/100 g
INACTIVE INGREDIENTS: SODIUM DODECYLBENZENESULFONATE; PROPYLENE GLYCOL; OLEA EUROPAEA (OLIVE) FRUIT OIL; SORBITOL; WATER; MELALEUCA ALTERNIFOLIA (TEA TREE) LEAF OIL; MYRISTIC ACID; SODIUM MYRISTATE; COCOS NUCIFERA (COCONUT) OIL; SODIUM HYDROXIDE; HAMAMELIS VIRGINIANA BARK; GLYCERIN; LAURIC ACID; ELAEIS GUINEENSIS (PALM) OIL; SULFUR; STEARIC ACID; SODIUM GLUTAMATE

Initial Drug Listing - Athlete's Foot Soap Bar

ACTIVE INGREDIENT

Tolnaftate 1%

PURPOSE

Antifungal

INDICATIONS AND USAGE

Helps relieve and prevent itching, burning, cracking, and scaling associated with fungal infections such as athlete's foot, jock itch, ringworm, and other skin irritations.

WARNINGS

For external use only

Do not use on children under 2 years of age unless directed by a doctor.

When using this product avoid contact with eyes, if contact occurs, rinse thoroughly with water.

Stop use and ask doctor if irritation occurs, there is no improvement within 2 weeks.

KEEP OUT OF REACH OF CHILDREN

if swallowed, get medical help or contact a Posion Control Center right away.

DOSAGE AND ADMINISTRATION

- Wash affected area & dry thoroughly.
- Apply a thin layer over affected area twice daily (morning and night).
- Supervise children in the use of this product.
- Use daily for 2 weeks.

INACTIVE INGREDIENT

Aqua (Water), Melaleuca Alternifolia (Tea Tree) Leaf Oil, Sorbitol, Elaeis Guineensis (Palm) Oil, Cocos Nucifera (Coconut) Oil, Olea Europaea (Olive) Fruit Oil, Propylene Glycol, Glycerin, Stearic Acid, Lauric Acid, Myristic Acid, Sodium Myristate, Sodium Glutamate, Sodium Hydroxide, Sodium Dodecylbenzene Sulfonate, Sulfur Thermal Water, Hamamelis Virginiana (Witch Hazel) Extract, Ceramide

OTHER SAFETY INFORMATION

Store at room temperature. Protect from excessive heat (above 104ºF /40ºC)

QUESTIONS

visit us at www.hermonhealth.com